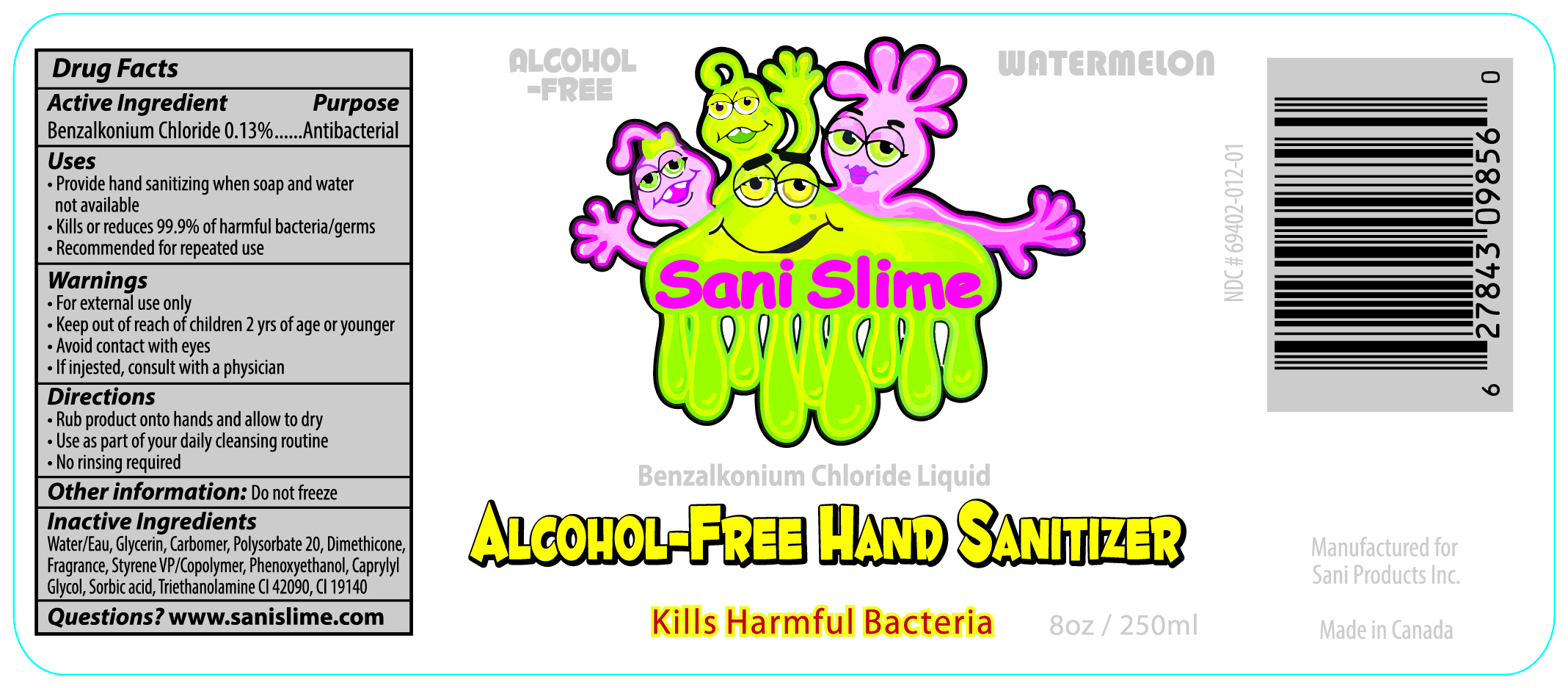 DRUG LABEL: BENZALKONIUM CHLORIDE
NDC: 69402-012 | Form: LIQUID
Manufacturer: SANI PRODUCTS INC.
Category: otc | Type: HUMAN OTC DRUG LABEL
Date: 20141213

ACTIVE INGREDIENTS: BENZALKONIUM CHLORIDE .13 g/1 mL
INACTIVE INGREDIENTS: GLYCERIN; POLYSORBATE 20; TROLAMINE; PHENOXYETHANOL; CAPRYLYL GLYCOL; SORBIC ACID; WATER; DIMETHICONE

SANI SLIME ALCOHOL-FREE HAND SANITIZER WATERMELON

ACTIVE INGREDIENTS

BENZALKONIUM CHLORIDE 0.13%

PURPOSE

ANTIBACTERIAL

USES

PROVIDE HAND SANITIZING WHEN SOAP AND WATER NOT AVAILABLE

KILLS OR REDUCES 99.9% OF HARMFUL BACTERIA/GERMS

RECOMMENDED FOR REPEATED USE

WARNINGS

FOR EXTERNAL USE ONLY

AVOID CONTACT WIYH EYES

IF INGESTED, CONSULT WITH A PHYSICIAN

WARNINGS

KEEP OUT OF REACH OF CHILDREN 2 YRS OF AGE OR YOUNGER

DIRECTIONS

RUB PRODUCT ONTO HANDS AND ALLOW TO DRY

USE AS PART OF YOUR DAILY CLEANSING ROUTINE

NO RINSING REQUIRED

QUESTIONS

WWW.SANISLIME.COM

OTHER INFORMATION

DO NOT FREEZE

INACTIVE INGREDIENT

WATER, GLYCERIN, CARBOMER, POLYSORBATE 20, DIMETHICONE, PHENOXYETHANOL, CAPRYLYL GLYCOL, SORBIC ACID, TRIETHANOLAMINE

SANISLIME ALCOHOL FREE HAND SANITIZER WATERMELON

ALCOHOL FREE

BENZALKONIUM CHLORIDE LIQUID

WATERMELON

SANISLIME

ALCOHOL-FREE HAND SANITIZER

KILLS HARMFUL BACTERIA

8 OZ (250 ML)